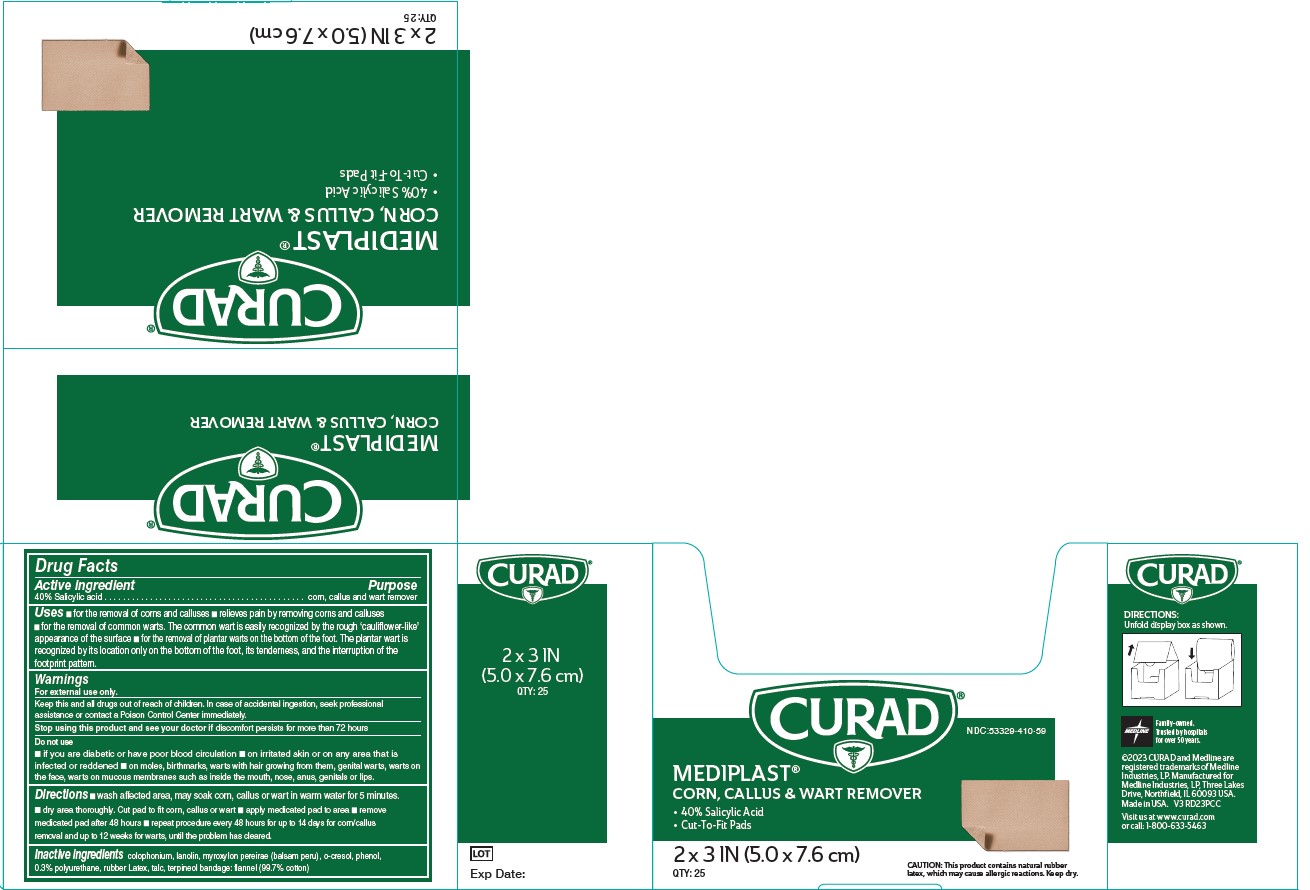 DRUG LABEL: MediPlast
NDC: 53329-410 | Form: PLASTER
Manufacturer: Medline Industries, LP
Category: otc | Type: HUMAN OTC DRUG LABEL
Date: 20241204

ACTIVE INGREDIENTS: SALICYLIC ACID 40 g/100 g
INACTIVE INGREDIENTS: PHENOL; LANOLIN; NATURAL LATEX RUBBER; BALSAM PERU; ROSIN; TALC; TERPINEOL; ORTHOCRESOL

410 Mediplast Corn, Callus & Wart Remover

Active ingredient

40% Salicylic Acid

Purpose

Corn, Callus, and Wart Remover

Uses

- for the removal of corns and calluses
- Relieves pain by removing corns and calluses
- for the removal of common warts. The common wart is easily recognized by the rough ‘cauliflower-like’ appearance of the surface
- for the removal of plantar warts on the bottom of the foot. The plantar wart is recognized by its location only on the bottom of the foot, its tenderness, and the interruption of the footprint pattern.

Warnings

For external use only. This product contains natural rubber, which may cause allergic reactions.

Keep this and all drugs out of reach of children.

In case of accidental ingestion, seek professional assistance or contact a Poison Control center immediately.

Stop using this product and see your doctor if

- discomfort persists for more than 72 hours

Do Not Use

- if you are diabetic or have poor blood circulation
- on irritated skin or on any area that is infected or reddened
- on moles, birthmarks, or warts with hair growing from them, genital warts, warts on the face, warts on mucous membranes such as warts inside the mouth, nose, anus, genitals or lips.

Directions

- Wash affected area. May soak corn, callus or wart in warm water for 5 minutes. Dry area thoroughly. Cut pad to fit corn, callus or wart. Apply medicated pad to area. Remove medicated pad after 48 hours. Repeat procedure every 48 hours for up to 14 days for corn/callus removal and up to 12 weeks for warts, until the problem has cleared.

Inactive ingredients

O-Cresol, Lanolin, Myroxylon pereirae (Balsam Peru), Phenol, Talc, Terpineol

Bandage: Flannel (99.7% cotton), Colophonium, Rubber Latex, 0.3% Polyurethane

RECENT MAJOR CHANGES

- Indications and Usage

Manufacturing Information

Manufactured for:

Medline Industries, LP

Three Lakes Drive, Northfield, IL 60093 USA

Made in USA

www.curad.com

1-800-633-5463

REF: CUR01496

V3 RD23PCC